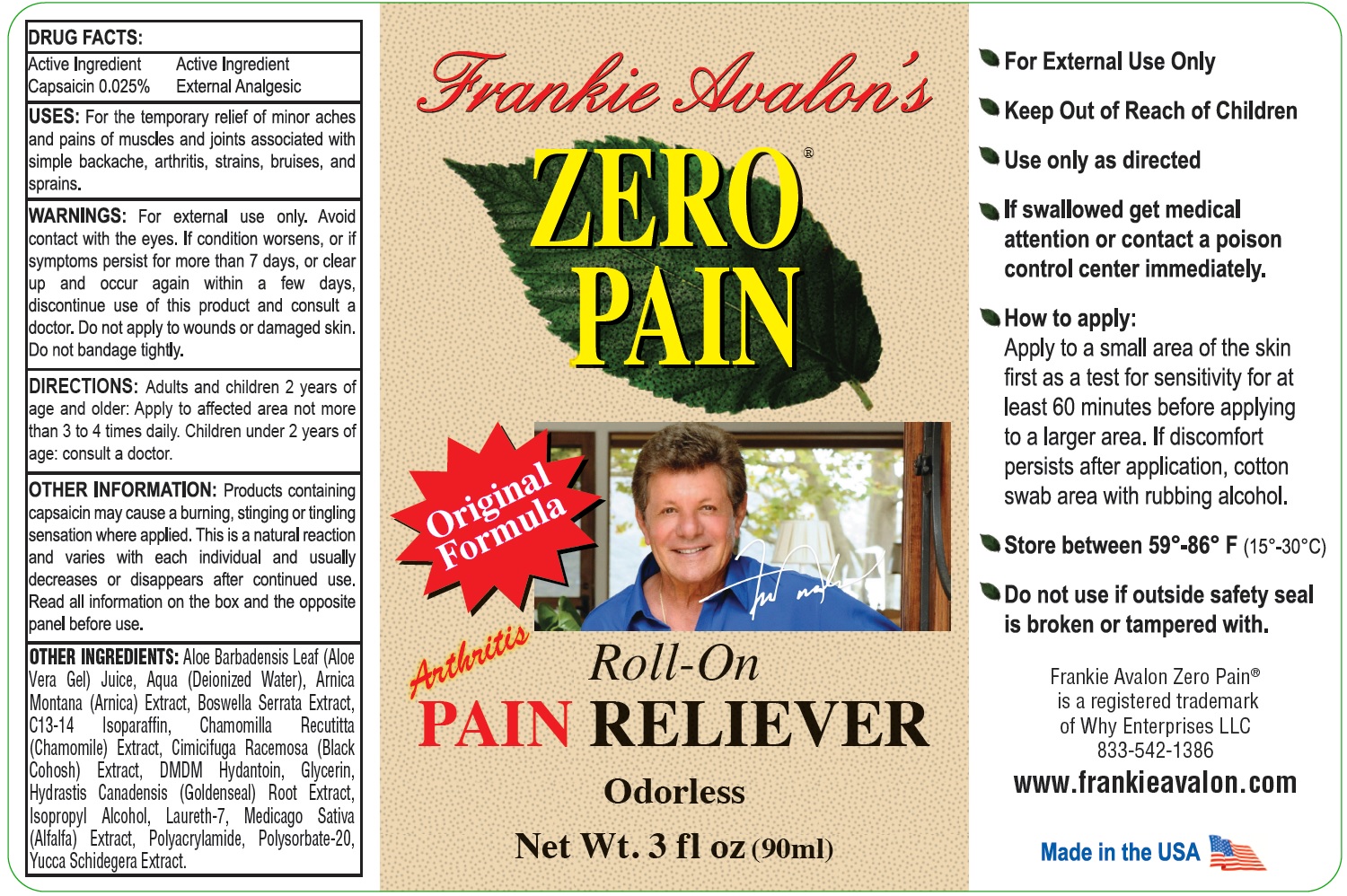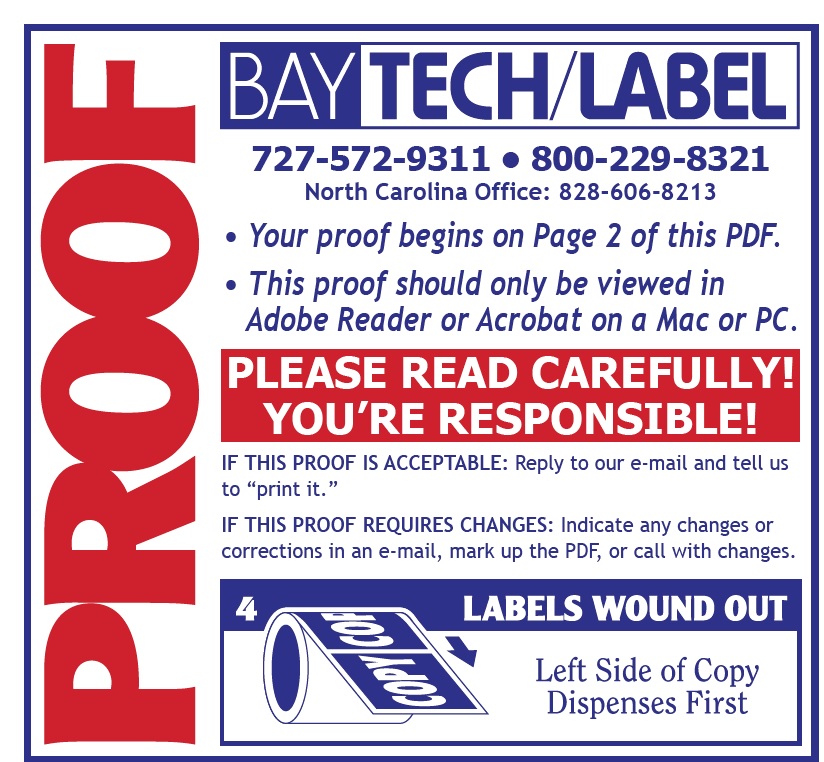 DRUG LABEL: Frankie Avalons ZERO PAIN Roll-On Pain Reliever
NDC: 84413-481 | Form: LIQUID
Manufacturer: WHY ENTERPRISES LLC
Category: otc | Type: HUMAN OTC DRUG LABEL
Date: 20240617

ACTIVE INGREDIENTS: CAPSAICIN 0.25 mg/1 mL
INACTIVE INGREDIENTS: ALOE VERA LEAF; WATER; ARNICA MONTANA FLOWER; INDIAN FRANKINCENSE; C13-14 ISOPARAFFIN; CHAMOMILE; BLACK COHOSH; DMDM HYDANTOIN; GLYCERIN; GOLDENSEAL; ISOPROPYL ALCOHOL; LAURETH-7; MEDICAGO SATIVA WHOLE; POLYSORBATE 20; YUCCA SCHIDIGERA WHOLE

Frankie Avalon's ZERO PAIN Roll-On Pain Reliever

Active Ingredient

Capsaicin 0.025%

PURPOSE

External Analgesic

USES:

For the temporary relief of minor aches and pains of muscles and joints associated with simple backache, arthritis, strains, bruises, and sprains.

WARNINGS:

For external use only. Avoid contact with the eyes. If condition worsens, or if symptoms persist for more than 7 days, or clear up and occur again within a few days, discontinue use of this product and consult a doctor. Do not apply to wounds or damaged skin. Do not bandage tightly.

DIRECTIONS:

Adults and children 2 years of age and older: Apply to affected area not more than 3 to 4 times daily. Children under 2 years of age: consult a doctor.

OTHER INFORMATION:

Products containing capsaicin may cause a burning, stinging or tingling sensation where applied. This is a natural reaction and varies with each individual and usually decreases or disappears after continued use. Read all information on the box and the opposite panel before use.

OTHER INGREDIENTS:

Aloe Barbadensis Leaf (Aloe Vera Gel) Juice, Aqua (Deionized Water), Arnica Montana (Arnica) Extract, Boswella Serrata Extract, C13-14 Isoparaffin, Chamomilla Recutitta (Chamomile) Extract, Cimicifuga Racemosa (Black Cohosh) Extract, DMDM Hydantoin, Glycerin, Hydrastis Canadensis (Goldenseal) Root Extract, Isopropyl Alcohol, Laureth-7, Medicago Sativa (Alfalfa) Extract, Polyacrylamide, Polysorbate-20, Yucca Schidegera Extract.